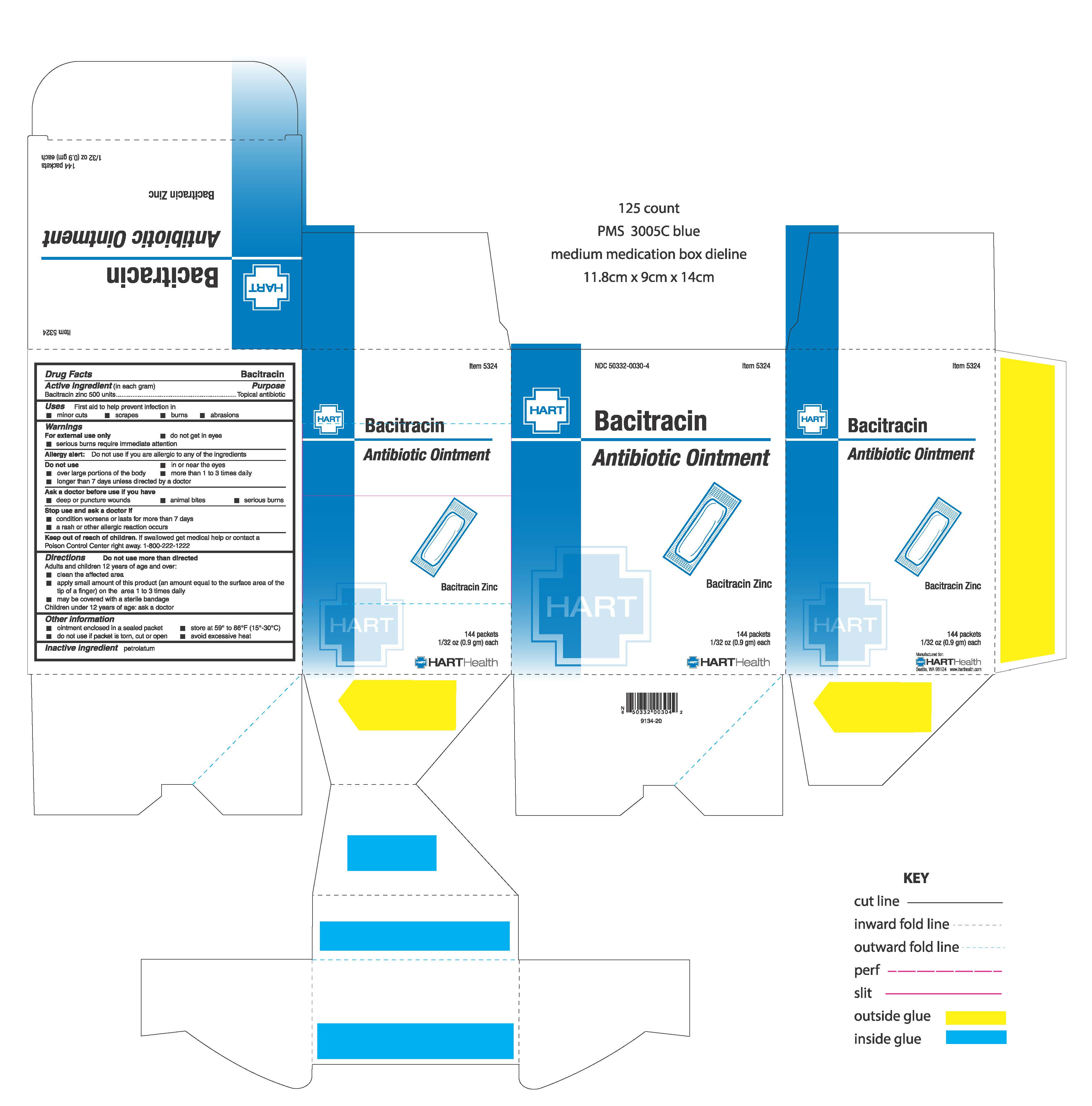 DRUG LABEL: BACITRACIN
NDC: 50332-0030 | Form: CREAM
Manufacturer: HART Health
Category: otc | Type: HUMAN OTC DRUG LABEL
Date: 20240124

ACTIVE INGREDIENTS: BACITRACIN ZINC 500 U/0.9 g
INACTIVE INGREDIENTS: PETROLATUM

Bacitracin Ointment

Active Ingredients (in each gram):

Bacitracin zinc 500 units

Purpose:

Topical Antibiotic

INDICATIONS AND USAGE

Uses: First aid to help prevent infection in

- minor cuts
- scrapes
- burns
- abrasions

Warnings: For external use only

- do not get in eyes
- serious burns require immediate attention

Allergy alert: do not use if you are allergic to any of the ingredients

Do not use:

- in or near the eyes
- over large portions of the body
- more than 1 to 3 times daily
- longer than 7 days unless directed by a doctor

Ask a doctor before use if you have

- deep or puncture wounds
- animal bites
- serious burns

Stop use and ask a doctor if

- condition worsens or lasts for more than 7 days
- a rash or other allergic reaction occurs

Keep out of reach of children. If swallowed get medical help or contact a Poison Control Center right away. 1-800-222-1222.

DOSAGE AND ADMINISTRATION

Directions: do not use more than directed

Adults and children 12 years of age and over:

- clean the affected area
- apply small amount of this product (an amount equal to the surface area of the tip of a finger) on the area 1 to 3 times daily
- may be covered with a sterile bandage

Children under 12 years of age: ask a doctor

Inactive Ingredients: petrolatum